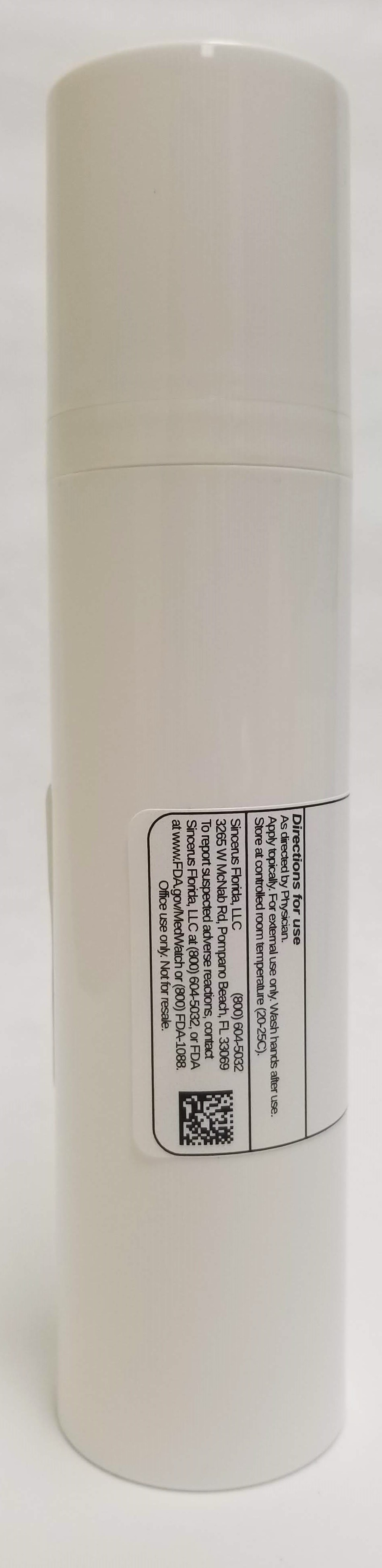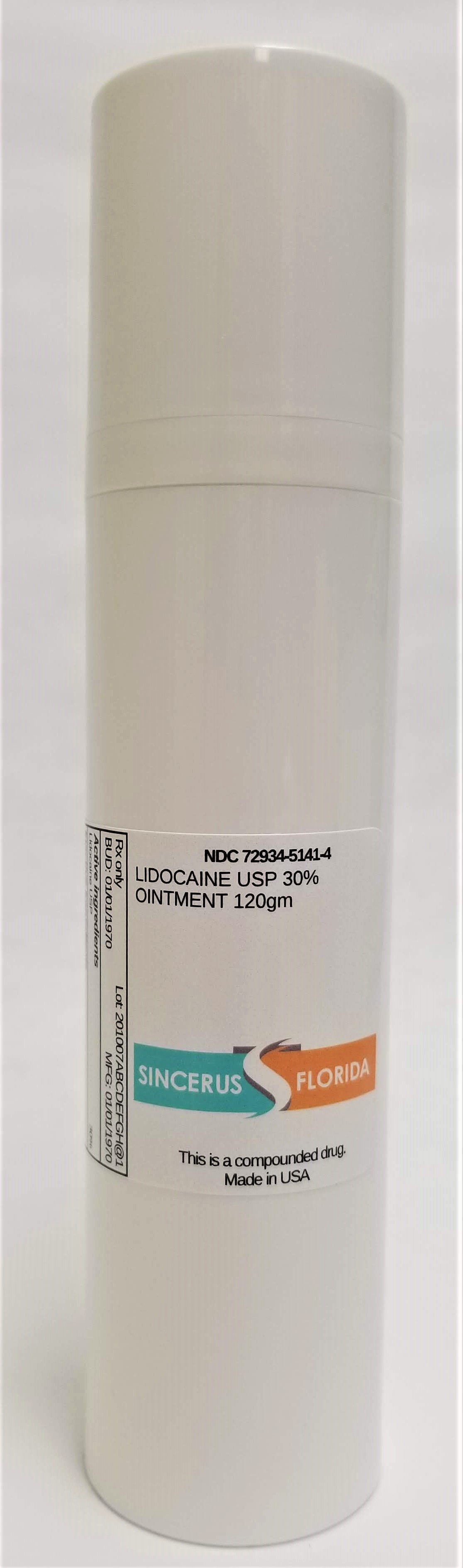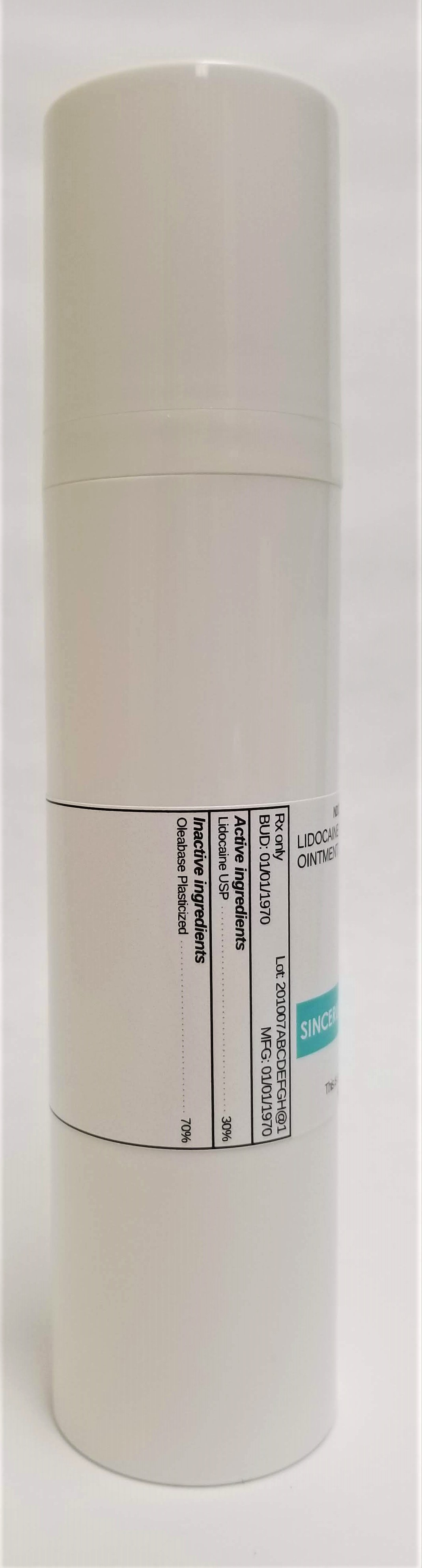 DRUG LABEL: LIDOCAINE 30%
NDC: 72934-5141 | Form: OINTMENT
Manufacturer: Sincerus Florida, LLC
Category: prescription | Type: HUMAN PRESCRIPTION DRUG LABEL
Date: 20190516

ACTIVE INGREDIENTS: LIDOCAINE 30 g/100 g

LIDOCAINE 30%